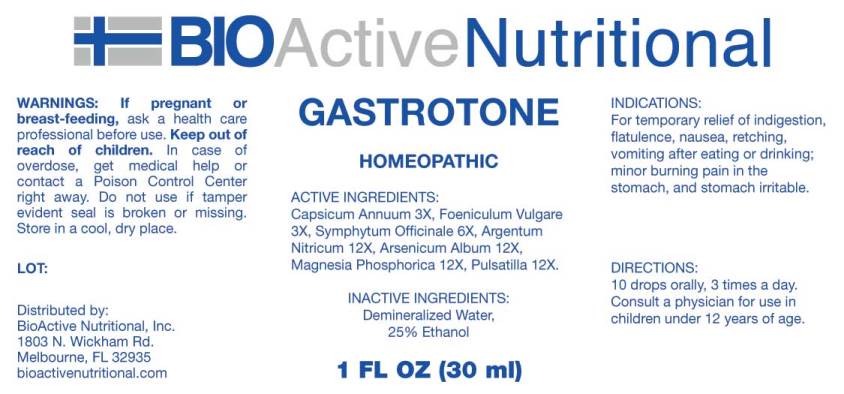 DRUG LABEL: Gastrotone
NDC: 43857-0458 | Form: LIQUID
Manufacturer: BioActive Nutritional, Inc.
Category: homeopathic | Type: HUMAN OTC DRUG LABEL
Date: 20170905

ACTIVE INGREDIENTS: CAPSICUM 3 [hp_X]/1 mL; FENNEL SEED 3 [hp_X]/1 mL; COMFREY ROOT 6 [hp_X]/1 mL; SILVER NITRATE 12 [hp_X]/1 mL; ARSENIC TRIOXIDE 12 [hp_X]/1 mL; MAGNESIUM PHOSPHATE, DIBASIC TRIHYDRATE 12 [hp_X]/1 mL; PULSATILLA VULGARIS 12 [hp_X]/1 mL
INACTIVE INGREDIENTS: WATER; ALCOHOL

Drug Facts:

ACTIVE INGREDIENTS:

Capsicum Annuum 3X, Foeniculum Vulgare 3X, Symphytum Officinale 3X, Argentum Nitricum 12X, Arsenicum Album 12X, Magnesia Phosphorica 12X, Pulsatilla (Vulgaris) 12X.

INDICATIONS:

For temporary relief of indigestion, flatulence, nausea, retching, vomitting after eating or drinking; minor burning pain in the stomach, and stomach irritable.

WARNINGS:

If pregnant or breast-feeding, ask a health care professional before use.

Keep out of reach of children. In case of overdose, get medical help or contact a Poison Control Center right away.

Do not use if tamper evident seal is broken or missing.

Store in cool, dry place.

Keep out of reach of children. In case of overdose, get medical help or contact a Poison Control Center right away.

DIRECTIONS:

10 drops orally, 3 times a day. Consult a physician for use in children under 12 years of age.

INDICATIONS:

For temporary relief of indigestion, flatulence, nausea, retching, vomitting after eating or drinking; minor burning pain in the stomach, and stomach irritable.

INACTIVE INGREDIENTS

Demineralized Water, 25% Ethanol.

QUESTIONS:

Distributed by:

BioActive Nutritional, Inc.

1803 N. Wickham Rd.

Melbourne, FL 32935

bioactivenutritional.com

PACKAGE LABEL DISPLAY:

BIOActive Nutritional

GASTROTONE

HOMEOPATHIC

1 FL OZ (30 ml)